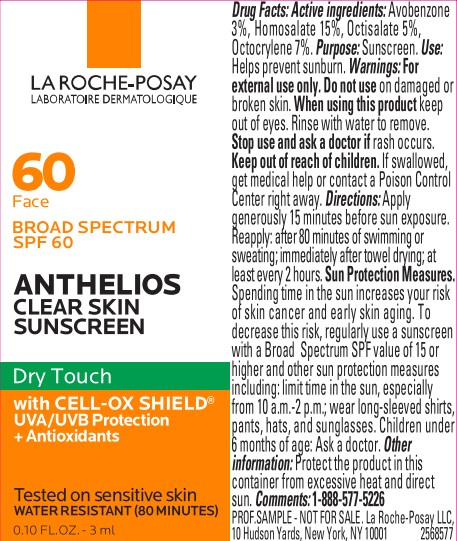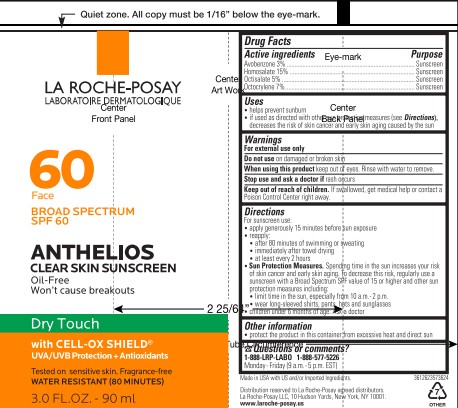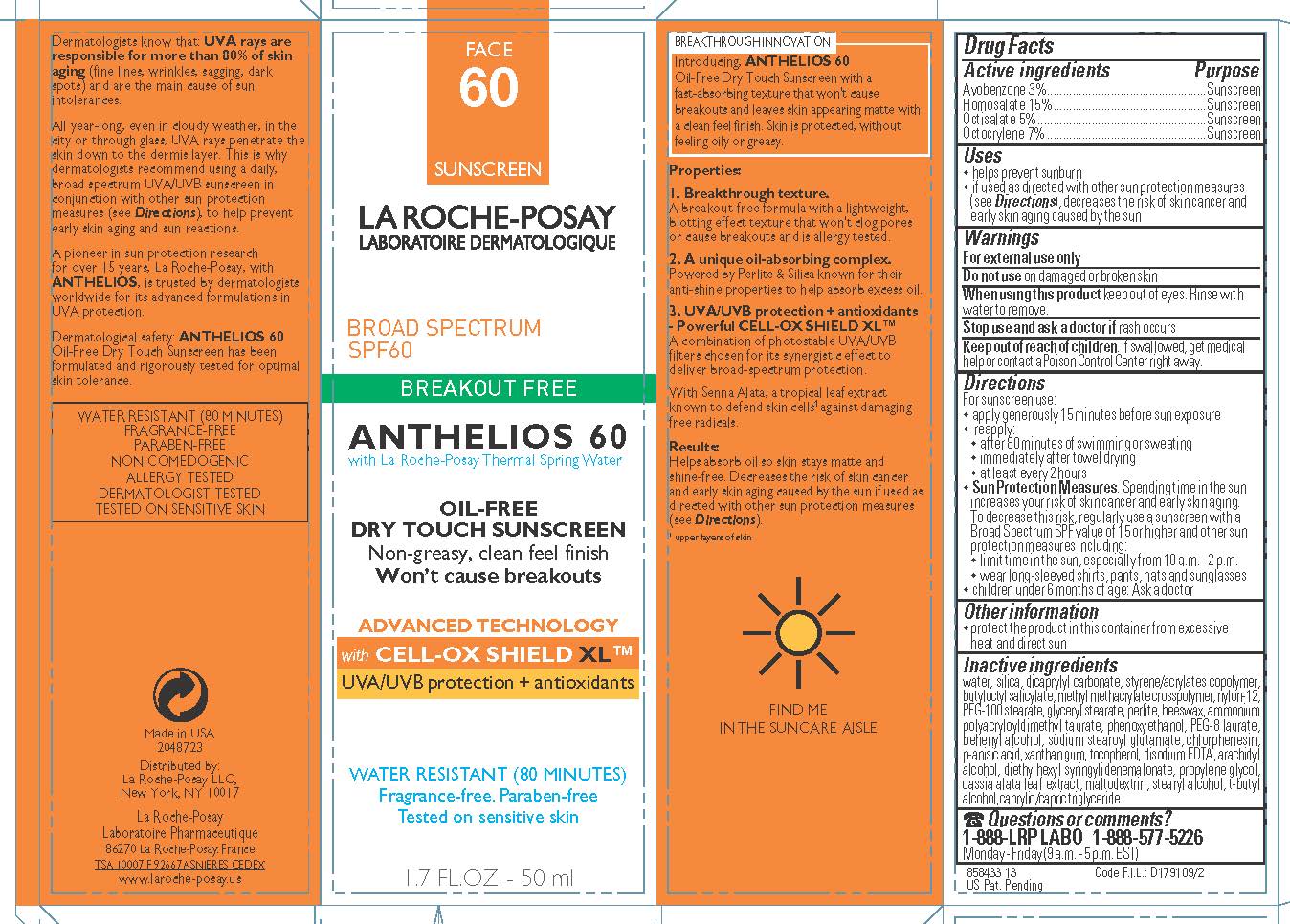 DRUG LABEL: La Roche Posay Laboratoire Dermatologique Anthelios 60 Breakout Free Oil Free Face Dry Touch Broad Spectrum SPF 60 Sunscreen Water Resistant 80 Minutes
NDC: 49967-994 | Form: LOTION
Manufacturer: L'Oreal USA Products Inc
Category: otc | Type: HUMAN OTC DRUG LABEL
Date: 20250710

ACTIVE INGREDIENTS: AVOBENZONE 30 mg/1 mL; HOMOSALATE 150 mg/1 mL; OCTISALATE 50 mg/1 mL; OCTOCRYLENE 70 mg/1 mL
INACTIVE INGREDIENTS: WATER; DICAPRYLYL CARBONATE; BUTYLOCTYL SALICYLATE; NYLON-12; PEG-100 STEARATE; PERLITE; PHENOXYETHANOL; PEG-8 LAURATE; SODIUM STEAROYL GLUTAMATE; CHLORPHENESIN; P-ANISIC ACID; XANTHAN GUM; TOCOPHEROL; ARACHIDYL ALCOHOL; DIETHYLHEXYL SYRINGYLIDENEMALONATE; PROPYLENE GLYCOL; MALTODEXTRIN; STEARYL ALCOHOL

Drug Facts

Active ingredient

Avobenzone 3%

Homosalate 15%

Octisalate 5%

Octocrylene 7%

Purpose

Sunscreen

Uses

- helps prevent sunburn
- if used as directed with other sun protection measures (see Directions), decreases the risk of skin cancer and early skin aging caused by the sun

Warnings

For external use only

Do not use

on damaged or broken skin

When using this product

keep out of eyes. Rinse with water to remove.

Stop use and ask a doctor if

rash occurs

Keep out of reach of children.

If swallowed, get medical help or contact a Poison Control Center right away.

Directions

For sunscreen use:

● apply generously 15 minutes before sun exposure

● reapply:

● after 80 minutes of swimming or sweating

● immediately after towel drying

● at least every 2 hours

● Sun Protection Measures. Spending time in the sun increases your risk of skin cancer and early skin aging. To decrease this risk, regularly use a sunscreen with a Broad Spectrum SPF value of 15 or higher and other sun protection measures including:

● limit time in the sun, especially from 10 a.m. – 2 p.m.

● wear long-sleeved shirts, pants, hats, and sunglasses

● children under 6 months of age: Ask a doctor

Other information

protect the product in this container from excessive heat and direct sun

Inactive ingredients

water, silica, dicaprylyl carbonate, styrene/acrylates copolymer, butyloctyl salicylate, methyl methacrylate crosspolymer, nylon-12, PEG-100 stearate, glyceryl stearate, perlite, beeswax, ammonium polyacryloyldimethyl taurate, phenoxyethanol, PEG-8 laurate, behenyl alcohol, sodium stearoyl glutamate, chlorphenesin, p-anisic acid, xanthan gum, tocopherol, disodium EDTA, arachidyl alcohol, diethylhexyl syringylidenemalonate, propylene glycol, cassia alata leaf extract, maltodextrin, stearyl alcohol, t-butyl alcohol, caprylic/capric triglyceride

Questions or comments?

1-888-LRP-LABO 1-888-577-5226

Monday - Friday (9 a.m. - 5 p.m. EST)